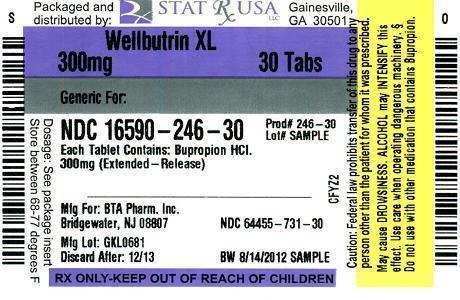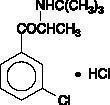 DRUG LABEL: WELLBUTRIN 
NDC: 16590-246 | Form: TABLET, EXTENDED RELEASE
Manufacturer: STAT Rx USA LLC
Category: prescription | Type: HUMAN PRESCRIPTION DRUG LABEL
Date: 20120822

ACTIVE INGREDIENTS: BUPROPION HYDROCHLORIDE 300 mg/1 1
INACTIVE INGREDIENTS: ETHYLCELLULOSES; GLYCERYL BEHENATE; METHACRYLIC ACID - ETHYL ACRYLATE COPOLYMER (1:1) TYPE A; POLYVINYL ALCOHOL; POLYETHYLENE GLYCOLS; POVIDONE; SILICON DIOXIDE; TRIETHYL CITRATE

WELLBUTRIN XL®
(bupropion hydrochloride extended-release tablets)

WARNING

Suicidality and Antidepressant Drugs

Use in Treating Psychiatric Disorders: Antidepressants increased the risk compared to placebo of suicidal thinking and behavior (suicidality) in children, adolescents, and young adults in short-term studies of major depressive disorder (MDD) and other psychiatric disorders. Anyone considering the use of WELLBUTRIN XL®* or any other antidepressant in a child, adolescent, or young adult must balance this risk with the clinical need. Short-term studies did not show an increase in the risk of suicidality with antidepressants compared to placebo in adults beyond age 24; there was a reduction in risk with antidepressants compared to placebo in adults aged 65 and older. Depression and certain other psychiatric disorders are themselves associated with increases in the risk of suicide. Patients of all ages who are started on antidepressant therapy should be monitored appropriately and observed closely for clinical worsening, suicidality, or unusual changes in behavior. Families and caregivers should be advised of the need for close observation and communication with the prescriber. WELLBUTRIN XL is not approved for use in pediatric patients. (See WARNINGS: Clinical Worsening and Suicide Risk in Treating Psychiatric Disorders, PRECAUTIONS: Information for Patients, and PRECAUTIONS: Pediatric Use.)

Use in Smoking Cessation Treatment: WELLBUTRIN®*, WELLBUTRIN SR and WELLBUTRIN XL are not approved for smoking cessation treatment, but bupropion under the name ZYBAN®* is approved for this use. Serious neuropsychiatric events, including but not limited to depression, suicidal ideation, suicide attempt, and completed suicide have been reported in patients taking bupropion for smoking cessation. Some cases may have been complicated by the symptoms of nicotine withdrawal in patients who stopped smoking. Depressed mood may be a symptom of nicotine withdrawal. Depression, rarely including suicidal ideation, has been reported in smokers undergoing a smoking cessation attempt without medication. However, some of these symptoms have occurred in patients taking bupropion who continued to smoke.

All patients treated with Bupropion for smoking cessation treatment should be observed for neuropsychiatric symptoms including changes in behavior, hostility, agitation, depressed mood, and suicide-related events, including ideation, behavior, and attempted suicide. These symptoms, as well as worsening of pre-existing psychiatric illness and completed suicide have been reported in some patients attempting to quit smoking while taking ZYBAN in the post-marketing experience. When symptoms were reported, most were during treatment with ZYBAN, but some were following discontinuation of treatment with ZYBAN. These events have occurred in patients with and without pre-existing psychiatric disease; some have experienced worsening of their psychiatric illnesses. Patients with serious psychiatric illness such as schizophrenia, bipolar disorder, and major depressive disorder did not participate in the pre-marketing studies of ZYBAN.

Advise patients and caregivers that the patient using bupropion for smoking cessation should stop taking bupropion and contact a healthcare provider immediately if agitation, hostility, depressed mood, or changes in thinking or behavior that are not typical for the patient are observed, or if the patient develops suicidal ideation or suicidal behavior. In many post-marketing cases, resolution of symptoms after discontinuation of ZYBAN was reported, although in some cases the symptoms persisted; therefore, ongoing monitoring and supportive care should be provided until symptoms resolve.

The risks of using bupropion for smoking cessation should be weighed against the benefits of its use. ZYBAN has been demonstrated to increase the likelihood of abstinence from smoking for as long as six months compared to treatment with placebo. The health benefits of quitting smoking are immediate and substantial. (See WARNINGS: Neuropsychiatric Symptoms and Suicide Risk in Smoking Cessation Treatment and PRECAUTIONS: Information for Patients.)

DESCRIPTION

WELLBUTRIN XL (bupropion hydrochloride), an antidepressant of the aminoketone class, is chemically unrelated to tricyclic, tetracyclic, selective serotonin re-uptake inhibitor, or other known antidepressant agents. Its structure closely resembles that of diethylpropion; it is related to phenylethylamines. It is designated as (±)-1-(3-chlorophenyl)-2-[(1,1-dimethylethyl)amino]-1-propanone hydrochloride. The molecular weight is 276.2. The molecular formula is C13H18ClNO•HCl. Bupropion hydrochloride powder is white, crystalline, and highly soluble in water. It has a bitter taste and produces the sensation of local anesthesia on the oral mucosa. The structural formula is:

WELLBUTRIN XL is supplied for oral administration as 150-mg and 300-mg, creamy-white to pale yellow extended-release tablets. Each tablet contains the labeled amount of bupropion hydrochloride and the inactive ingredients: ethylcellulose aqueous dispersion,glyceryl behenate, methacrylic acid copolymer dispersion, polyvinyl alcohol, polyethylene glycol, povidone, silicon dioxide, and triethyl citrate. The tablets are printed with edible black ink.

The insoluble shell of the extended-release tablet may remain intact during gastrointestinal transit and is eliminated in the feces.

CLINICAL PHARMACOLOGY

PHARMACODYNAMICS

Pharmacodynamics: Bupropion is a relatively weak inhibitor of the neuronal uptake of norepinephrine and dopamine, and does not inhibit monoamine oxidase or the re-uptake of serotonin. While the mechanism of action of bupropion, as with other antidepressants, is unknown, it is presumed that this action is mediated by noradrenergic and/or dopaminergic mechanisms.

PHARMACOKINETICS

Pharmacokinetics: Bupropion is a racemic mixture. The pharmacologic activity and pharmacokinetics of the individual enantiomers have not been studied. The mean elimination half-life (±SD) of bupropion after chronic dosing is 21 (±9) hours, and steady-state plasma concentrations of bupropion are reached within 8 days.

In a study comparing 14-day dosing with WELLBUTRIN XL 300 mg once daily to the immediate-release formulation of bupropion at 100 mg 3 times daily, equivalence was demonstrated for peak plasma concentration and area under the curve for bupropion and the 3 metabolites (hydroxybupropion, threohydrobupropion, and erythrohydrobupropion). Additionally, in a study comparing 14-day dosing with WELLBUTRIN XL 300 mg once daily to the sustained-release formulation of bupropion at 150 mg 2 times daily, equivalence was demonstrated for peak plasma concentration and area under the curve for bupropion and the 3 metabolites.

Absorption: Following oral administration of WELLBUTRIN XL to healthy volunteers, time to peak plasma concentrations for bupropion was approximately 5 hours and food did not affect the Cmax or AUC of bupropion.

Distribution: In vitro tests show that bupropion is 84% bound to human plasma proteins at concentrations up to 200 mcg/mL. The extent of protein binding of the hydroxybupropion metabolite is similar to that for bupropion, whereas the extent of protein binding of the threohydrobupropion metabolite is about half that seen with bupropion.

Metabolism: Bupropion is extensively metabolized in humans. Three metabolites have been shown to be active: hydroxybupropion, which is formed via hydroxylation of the tert-butyl group of bupropion, and the amino-alcohol isomers threohydrobupropion and erythrohydrobupropion, which are formed via reduction of the carbonyl group. In vitro findings suggest that cytochrome P450IIB6 (CYP2B6) is the principal isoenzyme involved in the formation of hydroxybupropion, while cytochrome P450 isoenzymes are not involved in the formation of threohydrobupropion. Oxidation of the bupropion side chain results in the formation of a glycine conjugate of meta-chlorobenzoic acid, which is then excreted as the major urinary metabolite. The potency and toxicity of the metabolites relative to bupropion have not been fully characterized. However, it has been demonstrated in an antidepressant screening test in mice that hydroxybupropion is one half as potent as bupropion, while threohydrobupropion and erythrohydrobupropion are 5-fold less potent than bupropion. This may be of clinical importance because the plasma concentrations of the metabolites are as high or higher than those of bupropion.

Because bupropion is extensively metabolized, there is the potential for drug-drug interactions, particularly with those agents that are metabolized by or which inhibit /induce the cytochrome P450IIB6 (CYP2B6) isoenzyme, such as ritonavir or efavirenz. In a healthy volunteer study, ritonavir at a dose of 100 mg twice daily reduced the AUC and C max of bupropion by 22% and 21%, respectively. The exposure of the hydroxybupropion metabolite was decreased by 23%, the threohydrobupropion decreased by 38%, and the erythrohydrobupropion decreased by 48%.

In a second healthy volunteer study, ritonavir at a dose of 600 mg twice daily decreased the AUC and the Cmax of bupropion by 66% and 62%, respectively. The exposure of the hydroxybupropion metabolite was decreased by 78%, the threohydrobupropion decreased by 50%, and the erythrohydrobupropion decreased by 68%.

In another healthy volunteer study, KALETRA® * (lopinavir 400 mg/ritonavir 100 mg twice daily) decreased bupropion AUC and C max by 57%. The AUC and Cmax of hydroxybupropion were decreased by 50% and 31%, respectively, (see PRECAUTIONS: Drug Interactions).

In a study in healthy volunteers, efzvirenz 600mg once daily for 2 weeks reduces the AUC and Cmax of bupropion by approximately 55% and 34%, respectively. The AUC of hydroxybupropion was unchanged, whereas Cmax of hydroxybupropion was increased by 50%.

Although bupropion is not metabolized by cytochrome P450IID6 (CYP2D6), there is the potential for drug-drug interactions when bupropion is coadministered with drugs metabolized by this isoenzyme (see PRECAUTIONS: Drug Interactions).

In humans, peak plasma concentrations of hydroxybupropion occur approximately 7 hours after administration of WELLBUTRIN XL. Following administration of WELLBUTRIN XL, peak plasma concentrations of hydroxybupropion are approximately 7 times the peak level of the parent drug at steady state. The elimination half-life of hydroxybupropion is approximately 20 (±5) hours, and its AUC at steady state is about 13 times that of bupropion. The times to peak concentrations for the erythrohydrobupropion and threohydrobupropion metabolites are similar to that of the hydroxybupropion metabolite. However, their elimination half-lives are longer, approximately 33 (±10) and 37 (±13) hours, respectively, and steady-state AUCs are 1.4 and 7 times that of bupropion, respectively.

Bupropion and its metabolites exhibit linear kinetics following chronic administration of 300 to 450 mg/day.

Elimination: Following oral administration of 200 mg of ^14C-bupropion in humans, 87% and 10% of the radioactive dose were recovered in the urine and feces, respectively. However, the fraction of the oral dose of bupropion excreted unchanged was only 0.5%, a finding consistent with the extensive metabolism of bupropion.

Population Subgroups: Factors or conditions altering metabolic capacity (e.g., liver disease, congestive heart failure [CHF], age, concomitant medications, etc.) or elimination may be expected to influence the degree and extent of accumulation of the active metabolites of bupropion. The elimination of the major metabolites of bupropion may be affected by reduced renal or hepatic function because they are moderately polar compounds and are likely to undergo further metabolism or conjugation in the liver prior to urinary excretion.

Hepatic: The effect of hepatic impairment on the pharmacokinetics of bupropion was characterized in 2 single-dose studies, one in patients with alcoholic liver disease and one in patients with mild to severe cirrhosis. The first study showed that the half-life of hydroxybupropion was significantly longer in 8 patients with alcoholic liver disease than in 8 healthy volunteers (32±14 hours versus 21±5 hours, respectively). Although not statistically significant, the AUCs for bupropion and hydroxybupropion were more variable and tended to be greater (by 53% to 57%) in patients with alcoholic liver disease. The differences in half-life for bupropion and the other metabolites in the 2 patient groups were minimal.

The second study showed no statistically significant differences in the pharmacokinetics of bupropion and its active metabolites in 9 patients with mild to moderate hepatic cirrhosis compared to 8 healthy volunteers. However, more variability was observed in some of the pharmacokinetic parameters for bupropion (AUC, Cmax, and Tmax) and its active metabolites (t½) in patients with mild to moderate hepatic cirrhosis. In addition, in patients with severe hepatic cirrhosis, the bupropion Cmax and AUC were substantially increased (mean difference: by approximately 70% and 3-fold, respectively) and more variable when compared to values in healthy volunteers; the mean bupropion half-life was also longer (29 hours in patients with severe hepatic cirrhosis vs 19 hours in healthy subjects). For the metabolite hydroxybupropion, the mean Cmax was approximately 69% lower. For the combined amino-alcohol isomers threohydrobupropion and erythrohydrobupropion, the mean Cmax was approximately 31% lower. The mean AUC increased by about 1½-fold for hydroxybupropion and about 2½-fold for threo/erythrohydrobupropion. The median Tmax was observed 19 hours later for hydroxybupropion and 31 hours later for threo/erythrohydrobupropion. The mean half-lives for hydroxybupropion and threo/erythrohydrobupropion were increased 5- and 2-fold, respectively, in patients with severe hepatic cirrhosis compared to healthy volunteers (see WARNINGS, PRECAUTIONS, and DOSAGE AND ADMINISTRATION).

Renal : There is limited information on the pharmacokinetics of bupropion in patients with renal impairment. An inter-study comparison between normal subjects and patients with end-stage renal failure demonstrated that the parent drug Cmax and AUC values were comparable in the 2 groups, whereas the hydroxybupropion and threohydrobupropion metabolites had a 2.3- and 2.8-fold increase, respectively, in AUC for patients with end-stage renal failure. A second study, comparing normal subjects and patients with moderate-to-severe renal impairment (GFR 30.9 ± 10.8 mL/min) showed that exposure to a single 150 mg dose sustained-release bupropion was approximately 2-fold higher in patients with impaired renal function while levels of the hydroxybupropion and threo/erythrohydrobupropion (combined) metabolites were similar in the 2 groups. The elimination of bupropion and/or the major metabolites of bupropion may be reduced by impaired renal function (see PRECAUTIONS: Renal Impairment).

Left Ventricular Dysfunction: During a chronic dosing study with bupropion in 14 depressed patients with left ventricular dysfunction (history of CHF or an enlarged heart on x-ray), no apparent effect on the pharmacokinetics of bupropion or its metabolites was revealed, compared to healthy volunteers.

Age: The effects of age on the pharmacokinetics of bupropion and its metabolites have not been fully characterized, but an exploration of steady-state bupropion concentrations from several depression efficacy studies involving patients dosed in a range of 300 to 750 mg/day, on a 3 times daily schedule, revealed no relationship between age (18 to 83 years) and plasma concentration of bupropion. A single-dose pharmacokinetic study demonstrated that the disposition of bupropion and its metabolites in elderly subjects was similar to that of younger subjects. These data suggest there is no prominent effect of age on bupropion concentration; however, another pharmacokinetic study, single and multiple dose, has suggested that the elderly are at increased risk for accumulation of bupropion and its metabolites (see PRECAUTIONS: Geriatric Use).

Gender: A single-dose study involving 12 healthy male and 12 healthy female volunteers revealed no sex-related differences in the pharmacokinetic parameters of bupropion.

Smokers: The effects of cigarette smoking on the pharmacokinetics of bupropion were studied in 34 healthy male and female volunteers; 17 were chronic cigarette smokers and 17 were nonsmokers. Following oral administration of a single 150-mg dose of bupropion, there was no statistically significant difference in Cmax, half-life, Tmax, AUC, or clearance of bupropion or its active metabolites between smokers and nonsmokers.

CLINICAL TRIALS

Major Depressive Disorder: The efficacy of bupropion as a treatment for major depressive disorder was established with the immediate-release formulation of bupropion in two 4-week, placebo-controlled trials in adult inpatients and in one 6-week, placebo-controlled trial in adult outpatients. In the first study, patients were titrated in a bupropion dose range of 300 to 600 mg/day of the immediate-release formulation on a 3 times daily schedule; 78% of patients received maximum doses of 450 mg/day or less. This trial demonstrated the effectiveness of bupropion on the Hamilton Depression Rating Scale (HDRS) total score, the depressed mood item (item 1) from that scale, and the Clinical Global Impressions (CGI) severity score. A second study included 2 fixed doses of the immediate-release formulation of bupropion (300 and 450 mg/day) and placebo. This trial demonstrated the effectiveness of bupropion, but only at the 450-mg/day dose of the immediate-release formulation; the results were positive for the HDRS total score and the CGI severity score, but not for HDRS item 1. In the third study, outpatients received 300 mg/day of the immediate-release formulation of bupropion. This study demonstrated the effectiveness of bupropion on the HDRS total score, HDRS item 1, the Montgomery-Asberg Depression Rating Scale, the CGI severity score, and the CGI improvement score.

In a longer-term study, outpatients meeting DSM-IV criteria for major depressive disorder, recurrent type, who had responded during an 8-week open trial on bupropion (150 mg twice daily of the sustained-release formulation) were randomized to continuation of their same dose of bupropion or placebo, for up to 44 weeks of observation for relapse. Response during the open phase was defined as CGI Improvement score of 1 (very much improved) or 2 (much improved) for each of the final 3 weeks. Relapse during the double-blind phase was defined as the investigator's judgment that drug treatment was needed for worsening depressive symptoms. Patients receiving continued bupropion treatment experienced significantly lower relapse rates over the subsequent 44 weeks compared to those receiving placebo.

Although there are no independent trials demonstrating the antidepressant effectiveness of WELLBUTRIN XL, studies have demonstrated similar bioavailability of WELLBUTRIN XL to both the immediate-release formulation and to the sustained-release formulation of bupropion under steady-state conditions, i.e., WELLBUTRIN XL 300 mg once daily was shown to have bioavailability that was similar to that of 100 mg 3 times daily of the immediate-release formulation of bupropion and to that of 150 mg 2 times daily of the sustained-release formulation of bupropion, with regard to both peak plasma concentration and extent of absorption, for parent drug and metabolites.

Seasonal Affective Disorder: The efficacy of WELLBUTRIN XL for the prevention of seasonal major depressive episodes associated with seasonal affective disorder was established in 3 double-blind, placebo-controlled trials in adult outpatients with a history of major depressive disorder with an autumn-winter seasonal pattern (as defined by DSM-IV criteria). Treatment was initiated prior to the onset of symptoms in the autumn (September to November) and was discontinued following a 2 week taper that began the first week of spring (fourth week of March), resulting in a treatment duration of approximately 4 to 6 months for the majority of patients. At the start of the study, patients were randomized to receive placebo or WELLBUTRIN XL 150 mg once daily for 1 week, followed by up-titration to 300 mg once daily. Patients who were deemed by the investigator to be unlikely or unable to tolerate 300 mg once daily were allowed to remain on, or had their dose reduced to, 150 mg once daily. The mean doses of WELLBUTRIN XL in the 3 studies ranged from 257 to 280 mg/day.

In these 3 trials, the percentage of patients who were depression-free at the end of treatment was significantly higher for WELLBUTRIN XL than for placebo: 81.4% vs 69.7%, 87.2% vs 78.7%, and 84.0% vs 69.0% for Study 1, 2 and 3, respectively; with a depression-free rate for the 3 studies combined of 84.3% vs 72.0%.

INDICATIONS AND USAGE

Major Depressive Disorder: WELLBUTRIN XL is indicated for the treatment of major depressive disorder.

The efficacy of bupropion in the treatment of a major depressive episode was established in two 4-week controlled trials of inpatients and in one 6-week controlled trial of outpatients whose diagnoses corresponded most closely to the Major Depression category of the APA Diagnostic and Statistical Manual (DSM) (see CLINICAL TRIALS).

A major depressive episode (DSM-IV) implies the presence of 1) depressed mood or 2) loss of interest or pleasure; in addition, at least 5 of the following symptoms have been present during the same 2-week period and represent a change from previous functioning: depressed mood, markedly diminished interest or pleasure in usual activities, significant change in weight and/or appetite, insomnia or hypersomnia, psychomotor agitation or retardation, increased fatigue, feelings of guilt or worthlessness, slowed thinking or impaired concentration, a suicide attempt, or suicidal ideation.

The efficacy of bupropion in maintaining an antidepressant response for up to 44 weeks following 8 weeks of acute treatment was demonstrated in a placebo-controlled trial with the sustained-release formulation of bupropion (see CLINICAL TRIALS). Nevertheless, the physician who elects to use WELLBUTRIN XL for extended periods should periodically reevaluate the long-term usefulness of the drug for the individual patient.

Seasonal Affective Disorder: WELLBUTRIN XL is indicated for the prevention of seasonal major depressive episodes in patients with a diagnosis of seasonal affective disorder.

The efficacy of WELLBUTRIN XL for the prevention of seasonal major depressive episodes was established in 3 controlled trials of adult outpatients with a history of major depressive disorder with an autumn-winter seasonal pattern as defined by Diagnostic and Statistical Manual of Mental Disorders, 4th edition (DSM-IV) criteria (see CLINICAL TRIALS).

Seasonal affective disorder is characterized by recurrent major depressive episodes, most commonly occurring during the autumn and/or winter months. Episodes may last up to 6 months in duration, typically beginning in the autumn and remitting in the springtime. Although patients with seasonal affective disorder may have depressive episodes during other times of the year, the diagnosis of seasonal affective disorder requires that the number of seasonal episodes substantially outnumber the number of non-seasonal episodes during the individual's lifetime.

CONTRAINDICATIONS

WELLBUTRIN XL is contraindicated in patients with a seizure disorder.

WELLBUTRIN XL is contraindicated in patients treated with ZYBAN® (bupropion hydrochloride) Sustained-Release Tablets; WELLBUTRIN® (bupropion hydrochloride), the immediate-release formulation; WELLBUTRIN SR, (bupropion hydrochloride), the sustained-release formulation; or any other medications that contain bupropion because the incidence of seizure is dose dependent.

WELLBUTRIN XL is contraindicated in patients with a current or prior diagnosis of bulimia or anorexia nervosa because of a higher incidence of seizures noted in patients treated for bulimia with the immediate-release formulation of bupropion.

WELLBUTRIN XL is contraindicated in patients undergoing abrupt discontinuation of alcohol or sedatives (including benzodiazepines).

The concurrent administration of WELLBUTRIN XL and a monoamine oxidase (MAO) inhibitor is contraindicated. At least 14 days should elapse between discontinuation of an MAO inhibitor and initiation of treatment with WELLBUTRIN XL.

WELLBUTRIN XL is contraindicated in patients who have shown an allergic response to bupropion or the other ingredients that make up WELLBUTRIN XL.

WARNINGS

Clinical Worsening and Suicide Risk in Treating Psychiatric Disorders: Patients with major depressive disorder (MDD), both adult and pediatric, may experience worsening of their depression and/or the emergence of suicidal ideation and behavior (suicidality) or unusual changes in behavior, whether or not they are taking antidepressant medications, and this risk may persist until significant remission occurs. Suicide is a known risk of depression and certain other psychiatric disorders, and these disorders themselves are the strongest predictors of suicide. There has been a long-standing concern, however, that antidepressants may have a role in inducing worsening of depression and the emergence of suicidality in certain patients during the early phases of treatment. Pooled analyses of short-term placebo-controlled trials of antidepressant drugs (SSRIs and others) showed that these drugs increase the risk of suicidal thinking and behavior (suicidality) in children, adolescents, and young adults (ages 18 to 24) with major depressive disorder (MDD) and other psychiatric disorders. Short-term studies did not show an increase in the risk of suicidality with antidepressants compared to placebo in adults beyond age 24; there was a reduction with antidepressants compared to placebo in adults aged 65 and older.

The pooled analyses of placebo-controlled trials in children and adolescents with MDD, obsessive compulsive disorder (OCD), or other psychiatric disorders included a total of 24 short-term trials of 9 antidepressant drugs in over 4,400 patients. The pooled analyses of placebo-controlled trials in adults with MDD or other psychiatric disorders included a total of 295 short-term trials (median duration of 2 months) of 11 antidepressant drugs in over 77,000 patients. There was considerable variation in risk of suicidality among drugs, but a tendency toward an increase in the younger patients for almost all drugs studied. There were differences in absolute risk of suicidality across the different indications, with the highest incidence in MDD. The risk differences (drug vs placebo), however, were relatively stable within age strata and across indications. These risk differences (drug-placebo difference in the number of cases of suicidality per 1,000 patients treated) are provided in Table 1.

Table 1
Age Range | Drug-Placebo Difference in Number of Cases of Suicidality per 1,000 Patients Treated
 | Increases Compared to Placebo
<18 | 14 additional cases
18-24 | 5 additional cases
 | Decreases Compared to Placebo
25-64 | 1 fewer case
≥65 | 6 fewer cases

No suicides occurred in any of the pediatric trials. There were suicides in the adult trials, but the number was not sufficient to reach any conclusion about drug effect on suicide.

It is unknown whether the suicidality risk extends to longer-term use, i.e., beyond several months. However, there is substantial evidence from placebo-controlled maintenance trials in adults with depression that the use of antidepressants can delay the recurrence of depression.

All patients being treated with antidepressants for any indication should be monitored appropriately and observed closely for clinical worsening, suicidality, and unusual changes in behavior, especially during the initial few months of a course of drug therapy, or at times of dose changes, either increases or decreases.

The following symptoms, anxiety, agitation, panic attacks, insomnia, irritability, hostility, aggressiveness, impulsivity, akathisia (psychomotor restlessness), hypomania, and mania, have been reported in adult and pediatric patients being treated with antidepressants for major depressive disorder as well as for other indications, both psychiatric and nonpsychiatric. Although a causal link between the emergence of such symptoms and either the worsening of depression and/or the emergence of suicidal impulses has not been established, there is concern that such symptoms may represent precursors to emerging suicidality.

Consideration should be given to changing the therapeutic regimen, including possibly discontinuing the medication, in patients whose depression is persistently worse, or who are experiencing emergent suicidality or symptoms that might be precursors to worsening depression or suicidality, especially if these symptoms are severe, abrupt in onset, or were not part of the patient's presenting symptoms.

Families and caregivers of patients being treated with antidepressants for major depressive disorder or other indications, both psychiatric and nonpsychiatric, should be alerted about the need to monitor patients for the emergence of agitation, irritability, unusual changes in behavior, and the other symptoms described above, as well as the emergence of suicidality, and to report such symptoms immediately to healthcare providers. Such monitoring should include daily observation by families and caregivers. Prescriptions for WELLBUTRIN XL should be written for the smallest quantity of tablets consistent with good patient management, in order to reduce the risk of overdose.

Neuropsychiatric Symptoms and Suicide Risk in Smoking Cessation Treatment:
WELLBUTRIN, WELLBUTRIN SR, and WELLBUTRIN XL are not approved for smoking cessation treatment, but bupropion under the name ZYBAN is approved for this use. Serious neuropsychiatric symptoms have been reported in patients taking bupropion for smoking cessation (see BOXED WARNING, ADVERSE REACTIONS). These have included changes in mood (including depression and mania), psychosis, hallucinations, paranoia, delusions, homicidal ideation, hostility, agitation, aggression, anxiety, and panic, as well as suicidal ideation, suicide attempt, and completed suicide. Some reported cases may have been complicated by the symptoms of nicotine withdrawal in patients who stopped smoking. Depressed mood may be a symptom of nicotine withdrawal. Depression, rarely including suicidal ideation, has been reported in smokers undergoing a smoking cessation attempt without medication. However, some of these symptoms have occurred in patients taking bupropion who continued to smoke. When symptoms were reported, most were during bupropion treatment, but some were following discontinuation of bupropion therapy.

These events have occurred in patients with and without pre-existing psychiatric disease; some have experienced worsening of their psychiatric illnesses. All patients being treated with bupropion as part of smoking cessation treatment should be observed for neuropsychiatric symptoms or worsening of pre-existing psychiatric illness.

Patients with serious psychiatric illness such as schizophrenia, bipolar disorder, and major depressive disorder did not participate in the pre-marketing studies of ZYBAN.

Advise patients and caregivers that the patient using bupropion for smoking cessation should stop taking bupropion and contact a healthcare provider immediately if agitation, depressed mood, or changes in behavior or thinking that are not typical for the patient are observed, or if the patient develops suicidal ideation or suicidal behavior. In many post-marketing cases, resolution of symptoms after discontinuation of ZYBAN was reported, although in some cases the symptoms persisted, therefore, ongoing monitoring and supportive care should be provided until symptoms resolve.

The risks of using bupropion for smoking cessation should be weighed against the benefits of its use. ZYBAN has been demonstrated to increase the likelihood of abstinence from smoking for as long as six months compared to treatment with placebo. The health benefits of quitting smoking are immediate and substantial.

Screening Patients for Bipolar Disorder: A major depressive episode may be the initial presentation of bipolar disorder. It is generally believed (though not established in controlled trials) that treating such an episode with an antidepressant alone may increase the likelihood of precipitation of a mixed/manic episode in patients at risk for bipolar disorder. Whether any of the symptoms described above represent such a conversion is unknown. However, prior to initiating treatment with an antidepressant, patients with depressive symptoms should be adequately screened to determine if they are at risk for bipolar disorder; such screening should include a detailed psychiatric history, including a family history of suicide, bipolar disorder, and depression. It should be noted that WELLBUTRIN XL is not approved for use in treating bipolar depression.

Bupropion-Containing Products: Patients should be made aware that WELLBUTRIN XL contains the same active ingredient found in ZYBAN, used as an aid to smoking cessation treatment, and that WELLBUTRIN XL should not be used in combination with ZYBAN, or any other medications that contain bupropion, such as WELLBUTRIN SR (bupropion hydrochloride), the sustained-release formulation or WELLBUTRIN (bupropion hydrochloride), the immediate-release formulation.

Seizures: Bupropion is associated with a dose-related risk of seizures. The risk of seizures is also related to patient factors, clinical situations, and concomitant medications, which must be considered in selection of patients for therapy with WELLBUTRIN XL. WELLBUTRIN XL should be discontinued and not restarted in patients who experience a seizure while on treatment.

As WELLBUTRIN XL is bioequivalent to both the immediate-release formulation of bupropion and to the sustained-release formulation of bupropion, the seizure incidence with WELLBUTRIN XL, while not formally evaluated in clinical trials, may be similar to that presented below for the immediate-release and sustained-release formulations of bupropion.

- Dose: At doses up to 300 mg/day of the sustained-release formulation of bupropion (WELLBUTRIN SR), the incidence of seizure is approximately 0.1% (1/1,000).

Data for the immediate-release formulation of bupropion revealed a seizure incidence of approximately 0.4% (i.e., 13 of 3,200 patients followed prospectively) in patients treated at doses in a range of 300 to 450 mg/day. This seizure incidence (0.4%) may exceed that of some other marketed antidepressants.

Additional data accumulated for the immediate-release formulation of bupropion suggested that the estimated seizure incidence increases almost tenfold between 450 and 600 mg/day. The 600 mg dose is twice the usual adult dose and one and one-third the maximum recommended daily dose (450 mg) of WELLBUTRIN XL. This disproportionate increase in seizure incidence with dose incrementation calls for caution in dosing.

- Patient factors: Predisposing factors that may increase the risk of seizure with bupropion use include history of head trauma or prior seizure, central nervous system (CNS) tumor, the presence of severe hepatic cirrhosis, and concomitant medications that lower seizure threshold.
- Clinical situations: Circumstances associated with an increased seizure risk include, among others, excessive use of alcohol or sedatives (including benzodiazepines); addiction to opiates, cocaine, or stimulants; use of over-the-counter stimulants and anorectics; and diabetes treated with oral hypoglycemics or insulin.
- Concomitant medications: Many medications (e.g., antipsychotics, antidepressants, theophylline, systemic steroids) are known to lower seizure threshold.

Recommendations for Reducing the Risk of Seizure: Retrospective analysis of clinical experience gained during the development of bupropion suggests that the risk of seizure may be minimized if

- the total daily dose of WELLBUTRIN XL does not exceed 450 mg,
- the rate of incrementation of dose is gradual.

WELLBUTRIN XL should be administered with extreme caution to patients with a history of seizure, cranial trauma, or other predisposition(s) toward seizure, or patients treated with other agents (e.g., antipsychotics, other antidepressants, theophylline, systemic steroids, etc.) that lower seizure threshold.

Hepatic Impairment: WELLBUTRIN XL should be used with extreme caution in patients with severe hepatic cirrhosis. In these patients a reduced frequency and/or dose is required as peak bupropion as well as AUC levels are substantially increased and accumulation is likely to occur in such patients to a greater extent than usual. The dose should not exceed 150 mg every other day in these patients (see CLINICAL PHARMACOLOGY, PRECAUTIONS, and DOSAGE AND ADMINISTRATION).

Potential for Hepatotoxicity: In rats receiving large doses of bupropion chronically, there was an increase in incidence of hepatic hyperplastic nodules and hepatocellular hypertrophy. In dogs receiving large doses of bupropion chronically, various histologic changes were seen in the liver, and laboratory tests suggesting mild hepatocellular injury were noted.

PRECAUTIONS

GENERAL PRECAUTIONS

General: Agitation and Insomnia: Increased restlessness, agitation, anxiety, and insomnia, especially shortly after initiation of treatment, have been associated with treatment with bupropion. In 3 placebo-controlled clinical trials of seasonal affective disorder with WELLBUTRIN XL, the incidence of agitation, anxiety, and insomnia are shown in Table 2.

Table 2. Incidence of Agitation, Anxiety, and Insomnia in Placebo-Controlled Trials of WELLBUTRIN XL for Seasonal Affective Disorder
Adverse Event Term | WELLBUTRIN XL; 150 to 300 mg/day; (n = 537) | Placebo; (n = 511)
Agitation | 2% | <1%
Anxiety | 7% | 5%
Insomnia | 20% | 13%

Patients in placebo-controlled trials of major depressive disorder with WELLBUTRIN SR, the sustained-release formulation of bupropion, experienced agitation, anxiety, and insomnia as shown in Table 3.

Table 3. Incidence of Agitation, Anxiety, and Insomnia in Placebo-Controlled Trials of WELLBUTRIN SR for Major Depressive Disorder
Adverse Event Term | WELLBUTRIN SR; 300 mg/day; (n = 376) | WELLBUTRIN SR; 400 mg/day; (n = 114) | Placebo; (n = 385)
Agitation | 3% | 9% | 2%
Anxiety | 5% | 6% | 3%
Insomnia | 11% | 16% | 6%

In clinical studies of major depressive disorder, these symptoms were sometimes of sufficient magnitude to require treatment with sedative/hypnotic drugs.

Symptoms in these studies were sufficiently severe to require discontinuation of treatment in 1% and 2.6% of patients treated with 300 and 400 mg/day, respectively, of bupropion sustained-release tablets and 0.8% of patients treated with placebo.

Psychosis, Confusion, and Other Neuropsychiatric Phenomena: Depressed patients treated with bupropion have been reported to show a variety of neuropsychiatric signs and symptoms, including delusions, hallucinations, psychosis, concentration disturbance, paranoia, and confusion. In some cases, these symptoms abated upon dose reduction and/or withdrawal of treatment.

Activation of Psychosis and/or Mania: Antidepressants can precipitate manic episodes in bipolar disorder patients during the depressed phase of their illness and may activate latent psychosis in other susceptible patients. WELLBUTRIN XL is expected to pose similar risks.

Altered Appetite and Weight: In 3 placebo-controlled clinical trials of seasonal affective disorder with WELLBUTRIN XL, the percentage of patients with weight gain or weight loss are shown in Table 4.

Table 4. Incidence of Weight Gain and Weight Loss in Placebo-Controlled Trials of WELLBUTRIN XL for Seasonal Affective Disorder
Weight Change | WELLBUTRIN XL; 150 to 300 mg/day; (n = 537) | Placebo; (n = 511)
Gained >5 lbs | 11% | 21%
Lost >5 lbs | 23% | 11%

In placebo-controlled studies of major depressive disorder using WELLBUTRIN SR, the sustained-release formulation of bupropion, patients experienced weight gain or weight loss as shown in Table 5.

Table 5. Incidence of Weight Gain and Weight Loss in Placebo-Controlled Trials of WELLBUTRIN SR for Major Depressive Disorder
Weight Change | WELLBUTRIN SR; 300 mg/day; (n = 339) | WELLBUTRIN SR; 400 mg/day; (n = 112) | Placebo; (n = 347)
Gained >5 lbs | 3% | 2% | 4%
Lost >5 lbs | 14% | 19% | 6%

In studies conducted with the immediate-release formulation of bupropion, 35% of patients receiving tricyclic antidepressants gained weight, compared to 9% of patients treated with the immediate-release formulation of bupropion. If weight loss is a major presenting sign of a patient's depressive illness, the anorectic and/or weight-reducing potential of WELLBUTRIN XL should be considered.

Allergic Reactions: Anaphylactoid/anaphylactic reactions characterized by symptoms such as pruritus, urticaria, angioedema, and dyspnea requiring medical treatment have been reported in clinical trials with bupropion. In addition, there have been rare spontaneous postmarketing reports of erythema multiforme, Stevens-Johnson syndrome, and anaphylactic shock associated with bupropion. A patient should stop taking WELLBUTRIN XL and consult a doctor if experiencing allergic or anaphylactoid/anaphylactic reactions (e.g., skin rash, pruritus, hives, chest pain, edema, and shortness of breath) during treatment.

Arthralgia, myalgia, and fever with rash and other symptoms suggestive of delayed hypersensitivity have been reported in association with bupropion. These symptoms may resemble serum sickness.

Cardiovascular Effects: In clinical practice, hypertension, in some cases severe, requiring acute treatment, has been reported in patients receiving bupropion alone and in combination with nicotine replacement therapy. These events have been observed in both patients with and without evidence of preexisting hypertension.

Data from a comparative study of the sustained-release formulation of bupropion (ZYBAN® Sustained-Release Tablets), nicotine transdermal system (NTS), the combination of sustained-release bupropion plus NTS, and placebo as an aid to smoking cessation suggest a higher incidence of treatment-emergent hypertension in patients treated with the combination of sustained-release bupropion and NTS. In this study, 6.1% of patients treated with the combination of sustained-release bupropion and NTS had treatment-emergent hypertension compared to 2.5%, 1.6%, and 3.1% of patients treated with sustained-release bupropion, NTS, and placebo, respectively. The majority of these patients had evidence of preexisting hypertension. Three patients (1.2%) treated with the combination of ZYBAN and NTS and 1 patient (0.4%) treated with NTS had study medication discontinued due to hypertension compared to none of the patients treated with ZYBAN or placebo. Monitoring of blood pressure is recommended in patients who receive the combination of bupropion and nicotine replacement.

There is no clinical experience establishing the safety of WELLBUTRIN XL in patients with a recent history of myocardial infarction or unstable heart disease. Therefore, care should be exercised if it is used in these groups. Bupropion was well tolerated in depressed patients who had previously developed orthostatic hypotension while receiving tricyclic antidepressants, and was also generally well tolerated in a group of 36 depressed inpatients with stable congestive heart failure (CHF). However, bupropion was associated with a rise in supine blood pressure in the study of patients with CHF, resulting in discontinuation of treatment in 2 patients for exacerbation of baseline hypertension.

Hepatic Impairment: WELLBUTRIN XL should be used with extreme caution in patients with severe hepatic cirrhosis. In these patients, a reduced frequency and/or dose is required. WELLBUTRIN XL should be used with caution in patients with hepatic impairment (including mild-to-moderate hepatic cirrhosis) and reduced frequency and/or dose should be considered in patients with mild-to-moderate hepatic cirrhosis.

All patients with hepatic impairment should be closely monitored for possible adverse effects that could indicate high drug and metabolite levels (see CLINICAL PHARMACOLOGY, WARNINGS, and DOSAGE AND ADMINISTRATION).

Renal Impairment: There is limited information on the pharmacokinetics of bupropion in patients with renal impairment. An inter-study comparison between normal subjects and patients with end-stage renal failure demonstrated that the parent drug Cmax and AUC values were comparable in the 2 groups, whereas the hydroxybupropion and threohydrobupropion metabolites had a 2.3– and 2.8-fold increase, respectively, in AUC for patients with end-stage renal failure. A second study, comparing normal subjects and patients with moderate-to-severe renal impairment (GFR 30.9 ± 10.8 mL/min) showed that exposure to a single 150 mg dose of sustained-release bupropion was approximately 2-fold higher in patients with impaired renal function while levels of the hydroxybupropion and threo/erythrohydrobupropion (combined) metabolites were similar in the 2 groups. Bupropion is extensively metabolized in the liver to active metabolites, which are further metabolized and subsequently excreted by the kidneys. WELLBUTRIN XL should be used with caution in patients with renal impairment and a reduced frequency and/or dose should be considered as bupropion and the metabolites of bupropion may accumulate in such patients to a greater extent than usual. The patient should be closely monitored for possible adverse effects that could indicate high drug or metabolite levels.

PATIENT COUNSELING INFORMATION

Information for Patients: Prescribers or other health professionals should inform patients, their families, and their caregivers about the benefits and risks associated with treatment with WELLBUTRIN XL and should counsel them in its appropriate use. A patient Medication Guide about "Antidepressant Medicines, Depression and Other Serious Mental Illnesses, and Suicidal Thoughts or Actions", "Quitting Smoking, Quit-Smoking Medications, Changes in Thinking and Behavior, Depression, and Suicidal Thoughts or Actions", and "What Other Important Information Should I Know About WELLBUTRIN XL?" is available for WELLBUTRIN XL. The prescriber or health professional should instruct patients, their families, and their caregivers to read the Medication Guide and should assist them in understanding its contents. Patients should be given the opportunity to discuss the contents of the Medication Guide and to obtain answers to any questions they may have. The complete text of the Medication Guide is reprinted at the end of this document.

Patients should be advised of the following issues and asked to alert their prescriber if these occur while taking WELLBUTRIN XL.

Clinical Worsening and Suicide Risk in Treating Psychiatric Disorders: Patients, their families, and their caregivers should be encouraged to be alert to the emergence of anxiety, agitation, panic attacks, insomnia, irritability, hostility, aggressiveness, impulsivity, akathisia (psychomotor restlessness), hypomania, mania, other unusual changes in behavior, worsening of depression, and suicidal ideation, especially early during antidepressant treatment and when the dose is adjusted up or down. Families and caregivers of patients should be advised to look for the emergence of such symptoms on a day-to-day basis, since changes may be abrupt. Such symptoms should be reported to the patient's prescriber or health professional, especially if they are severe, abrupt in onset, or were not part of the patient's presenting symptoms. Symptoms such as these may be associated with an increased risk for suicidal thinking and behavior and indicate a need for very close monitoring and possibly changes in the medication.

Neuropsychiatric Symptoms and Suicide Risk in Smoking Cessation Treatment: Although WELLBUTRIN XL is not indicated for smoking cessation treatment, it contains the same active ingredient as ZYBAN which is approved for this use. Patients should be informed that quitting smoking, with or without ZYBAN, may be associated with nicotine withdrawal symptoms (including depression or agitation), or exacerbation of pre-existing psychiatric illness. Furthermore some patients have experienced changes in mood (including depression and mania), psychosis, hallucinations, paranoia, delusions, homicidal ideation, aggression, anxiety, and panic, as well as suicidal ideation, suicide attempt, and completed suicide when attempting to quit smoking while taking ZYBAN. If patients develop agitation, hostility, depressed mood, or changes in thinking or behavior that are not typical for them, or if patients develop suicidal ideation or behavior, they should be urged to report these symptoms to their healthcare provider immediately

Bupropion-Containing Products: Patients should be made aware that WELLBUTRIN XL contains the same active ingredient found in ZYBAN, used as an aid to smoking cessation treatment, and that WELLBUTRIN XL should not be used in combination with ZYBAN or any other medications that contain bupropion hydrochloride (such as WELLBUTRIN SR, the sustained-release formulation, and WELLBUTRIN, the immediate-release formulation).

Patients should be told that WELLBUTRIN XL should be discontinued and not restarted if they experience a seizure while on treatment.

Patients should be told that any CNS-active drug like WELLBUTRIN XL may impair their ability to perform tasks requiring judgment or motor and cognitive skills. Consequently, until they are reasonably certain that WELLBUTRIN XL does not adversely affect their performance, they should refrain from driving an automobile or operating complex, hazardous machinery.

Patients should be told that the excessive use or abrupt discontinuation of alcohol or sedatives (including benzodiazepines) may alter the seizure threshold. Some patients have reported lower alcohol tolerance during treatment with WELLBUTRIN XL. Patients should be advised that the consumption of alcohol should be minimized or avoided.

Patients should be advised to inform their physicians if they are taking or plan to take any prescription or over-the-counter drugs. Concern is warranted because WELLBUTRIN XL and other drugs may affect each other's metabolism.

Patients should be advised to notify their physicians if they become pregnant or intend to become pregnant during therapy.

Patients should be advised to swallow WELLBUTRIN XL whole so that the release rate is not altered. Do not chew, divide, or crush tablets, as this may lead to an increased risk of adverse effects, including seizures.

Patients should be advised that they may notice in their stool something that looks like a tablet. This is normal. The medication in WELLBUTRIN XL is contained in a non-absorbable shell that has been specially designed to slowly release drug in the body. When this process is completed, the empty shell is eliminated from the body.

LABORATORY TESTS

Laboratory Tests: There are no specific laboratory tests recommended.

DRUG INTERACTIONS

Drug Interactions: Few systemic data have been collected on the metabolism of bupropion following concomitant administration with other drugs or, alternatively, the effect of concomitant administration of bupropion on the metabolism of other drugs.

Because bupropion is extensively metabolized, the coadministration of other drugs may affect its clinical activity. In vitro studies indicate that bupropion is primarily metabolized to hydroxybupropion by the CYP2B6 isoenzyme. Therefore, the potential exists for a drug interaction between WELLBUTRIN XL and drugs that are substrates of or inhibitors /inducers of the CYP2B6 isoenzyme (e.g., orphenadrine, thiotepa, cyclophosphamide, ticlopidine, and clopidogrel). In addition, in vitro studies suggest that paroxetine, sertraline, norfluoxetine, and fluvoxamine as well as nelfinavir and efavirenz inhibit the hydroxylation of bupropion. No clinical studies have been performed to evaluate this finding. The threohydrobupropion metabolite of bupropion does not appear to be produced by the cytochrome P450 isoenzymes. The effects of concomitant administration of cimetidine on the pharmacokinetics of bupropion and its active metabolites were studied in 24 healthy young male volunteers. Following oral administration of two 150-mg tablets of the sustained-release formulation of bupropion with and without 800 mg of cimetidine, the pharmacokinetics of bupropion and hydroxybupropion were unaffected. However, there were 16% and 32% increases in the AUC and Cmax, respectively, of the combined moieties of threohydrobupropion and erythrohydrobupropion.

In a series of studies in healthy volunteers, ritonavir (100 mg twice daily or 600 mg twice daily) or ritonavir 100 mg plus lopinavir (KALETRA) 400 mg twice daily reduced the exposure of bupropion and its major metabolites in a dose dependent manner by approximately 20% to 80%. Similarly, efavirenz 600mg once daily for 2 weeks reduced the exposure of bupropion by approximately 55%. This effect of ritonavir, KALETRA, and efavirenz is thought to be due to the induction of bupropion metabolism. Patients receiving any of these drugs with bupropion may need increased doses of bupropion, but the maximum recommended dose of bupropion should not be exceeded (see CLINICAL PHARMACOLOGY: Metabolism).

While not systematically studied, certain drugs may induce the metabolism of bupropion (e.g., carbamazepine, phenobarbital, phenytoin).

Multiple oral doses of bupropion had no statistically significant effects on the single dose pharmacokinetics of lamotrigine in 12 healthy volunteers.

Animal data indicated that bupropion may be an inducer of drug-metabolizing enzymes in humans. In one study, following chronic administration of bupropion, 100 mg 3 times daily to 8 healthy male volunteers for 14 days, there was no evidence of induction of its own metabolism. Nevertheless, there may be the potential for clinically important alterations of blood levels of coadministered drugs.

Drugs Metabolized By Cytochrome P450IID6 (CYP2D6): Many drugs, including most antidepressants (SSRIs, many tricyclics), beta-blockers, antiarrhythmics, and antipsychotics are metabolized by the CYP2D6 isoenzyme. Although bupropion is not metabolized by this isoenzyme, bupropion and hydroxybupropion are inhibitors of CYP2D6 isoenzyme in vitro. In a study of 15 male subjects (ages 19 to 35 years) who were extensive metabolizers of the CYP2D6 isoenzyme, daily doses of bupropion given as 150 mg twice daily followed by a single dose of 50 mg desipramine increased the Cmax, AUC, and t1/2 of desipramine by an average of approximately 2-, 5-, and 2-fold, respectively. The effect was present for at least 7 days after the last dose of bupropion. Concomitant use of bupropion with other drugs metabolized by CYP2D6 has not been formally studied.

Therefore, coadministration of bupropion with drugs that are metabolized by CYP2D6 isoenzyme including certain antidepressants (e.g., nortriptyline, imipramine, desipramine, paroxetine, fluoxetine, sertraline), antipsychotics (e.g., haloperidol, risperidone, thioridazine), beta-blockers (e.g., metoprolol), and Type 1C antiarrhythmics (e.g., propafenone, flecainide), should be approached with caution and should be initiated at the lower end of the dose range of the concomitant medication. If bupropion is added to the treatment regimen of a patient already receiving a drug metabolized by CYP2D6, the need to decrease the dose of the original medication should be considered, particularly for those concomitant medications with a narrow therapeutic index.

Drugs which require metabolic activation by CYP2D6 in order to be effective (e.g., tamoxifen) theorectically could have reduced efficacy when administered concomitantly with inhibitors of CYP2D6 such as bupropion.

Although citalopram is not primarily metabolized by CYP2D6, in one study bupropion increased the Cmax and AUC of citalopram by 30% and 40%, respectively. Citalopram did not affect the pharmacokinetics of bupropion and its three metabolites.

MAO Inhibitors: Studies in animals demonstrate that the acute toxicity of bupropion is enhanced by the MAO inhibitor phenelzine (see CONTRAINDICATIONS).

Levodopa and Amantadine: Limited clinical data suggest a higher incidence of adverse experiences in patients receiving bupropion concurrently with either levodopa or amantadine. Administration of WELLBUTRIN XL to patients receiving either levodopa or amantadine concurrently should be undertaken with caution, using small initial doses and gradual dose increases.

Drugs That Lower Seizure Threshold: Concurrent administration of WELLBUTRIN XL and agents (e.g., antipsychotics, other antidepressants, theophylline, systemic steroids, etc.) that lower seizure threshold should be undertaken only with extreme caution (see WARNINGS). Low initial dosing and gradual dose increases should be employed.

Nicotine Transdermal System: (see PRECAUTIONS: Cardiovascular Effects).

Alcohol: In postmarketing experience, there have been rare reports of adverse neuropsychiatric events or reduced alcohol tolerance in patients who were drinking alcohol during treatment with bupropion. The consumption of alcohol during treatment with WELLBUTRIN XL should be minimized or avoided (also see CONTRAINDICATIONS).

Drug-Laboratory Test Interactions: False-positive urine immunoassay screening tests for amphetamines have been reported in patients taking bupropion. This is due to lack of specificity of some screening tests. False-positive test results may result even following discontinuation of bupropion therapy. Confirmatory tests, such as gas chromatography/mass spectrometry, will distinguish bupropion from amphetamines.

CARCINOGENESIS AND MUTAGENESIS AND IMPAIRMENT OF FERTILITY

Carcinogenesis, Mutagenesis, Impairment of Fertility: Lifetime carcinogenicity studies were performed in rats and mice at doses up to 300 and 150 mg/kg/day, respectively. These doses are approximately 7 and 2 times the maximum recommended human dose (MRHD), respectively, on a mg/m^2 basis. In the rat study there was an increase in nodular proliferative lesions of the liver at doses of 100 to 300 mg/kg/day (approximately 2 to 7 times the MRHD on a mg/m^2 basis); lower doses were not tested. The question of whether or not such lesions may be precursors of neoplasms of the liver is currently unresolved. Similar liver lesions were not seen in the mouse study, and no increase in malignant tumors of the liver and other organs was seen in either study.

Bupropion produced a positive response (2 to 3 times control mutation rate) in 2 of 5 strains in the Ames bacterial mutagenicity test and an increase in chromosomal aberrations in 1 of 3 in vivo rat bone marrow cytogenetic studies.

A fertility study in rats at doses up to 300 mg/kg/day revealed no evidence of impaired fertility.

PREGNANCY

TERATOGENIC EFFECTS

Pregnancy: Teratogenic Effects: Pregnancy Category C. In studies conducted in rats and rabbits, bupropion was administered orally at doses up to 450 and 150 mg/kg/day, respectively (approximately 11 and 7 times the maximum recommended human dose [MRHD], respectively, on a mg/m^2 basis), during the period of organogenesis. No clear evidence of teratogenic activity was found in either species; however, in rabbits, slightly increased incidences of fetal malformations and skeletal variations were observed at the lowest dose tested (25 mg/kg/day, approximately equal to the MRHD on a mg/m^2 basis) and greater. Decreased fetal weights were seen at 50 mg/kg and greater.

When rats were administered bupropion at oral doses of up to 300 mg/kg/day (approximately 7 times the MRHD on a mg/m^2 basis) prior to mating and throughout pregnancy and lactation, there were no apparent adverse effects on offspring development.

One study has been conducted in pregnant women. This retrospective, managed-care database study assessed the risk of congenital malformations overall, and cardiovascular malformations specifically, following exposure to bupropion in the first trimester compared to the risk of these malformations following exposure to other antidepressants in the first trimester and bupropion outside of the first trimester. This study included 7,005 infants with antidepressant exposure during pregnancy, 1,213 of whom were exposed to bupropion in the first trimester. The study showed no greater risk for congenital malformations overall, or cardiovascular malformations specifically, following first trimester bupropion exposure compared to exposure to all other antidepressants in the first trimester, or bupropion outside of the first trimester. The results of this study have not been corroborated. WELLBUTRIN XL should be used during pregnancy only if the potential benefit justifies the potential risk to the fetus.

Labor and Delivery: The effect of WELLBUTRIN XL Tablets on labor and delivery in humans is unknown.

NURSING MOTHERS

Nursing Mothers: Like many other drugs, bupropion and its metabolites are secreted in human milk. Because of the potential for serious adverse reactions in nursing infants from WELLBUTRIN XL, a decision should be made whether to discontinue nursing or to discontinue the drug, taking into account the importance of the drug to the mother.

PEDIATRIC USE

Pediatric Use: Safety and effectiveness in the pediatric population have not been established (see BOX WARNING and WARNINGS: Clinical Worsening and Suicide Risk in Treating Psychiatric Disorders). Anyone considering the use of WELLBUTRIN XL in a child or adolescent must balance the potential risks with the clinical need.

GERIATRIC USE

Geriatric Use: Of the approximately 6,000 patients who participated in clinical trials with bupropion sustained-release tablets (depression and smoking cessation studies), 275 were ≥65 years old and 47 were ≥75 years old. In addition, several hundred patients 65 and over participated in clinical trials using the immediate-release formulation of bupropion (depression studies). No overall differences in safety or effectiveness were observed between these subjects and younger subjects. Reported clinical experience has not identified differences in responses between the elderly and younger patients, but greater sensitivity of some older individuals cannot be ruled out.

A single-dose pharmacokinetic study demonstrated that the disposition of bupropion and its metabolites in elderly subjects was similar to that of younger subjects; however, another pharmacokinetic study, single and multiple dose, has suggested that the elderly are at increased risk for accumulation of bupropion and its metabolites (see CLINICAL PHARMACOLOGY).

Bupropion is extensively metabolized in the liver to active metabolites, which are further metabolized and excreted by the kidneys. The risk of toxic reaction to this drug may be greater in patients with impaired renal function. Because elderly patients are more likely to have decreased renal function, care should be taken in dose selection, and it may be useful to monitor renal function (see PRECAUTIONS: Renal Impairment and DOSAGE AND ADMINISTRATION).

ADVERSE REACTIONS (See also WARNINGS and PRECAUTIONS.)

Major Depressive Disorder: WELLBUTRIN XL has been demonstrated to have similar bioavailability both to the immediate-release formulation of bupropion and to the sustained-release formulation of bupropion (see CLINICAL PHARMACOLOGY). The information included under this subsection is based primarily on data from controlled clinical trials with WELLBUTRIN SR, the sustained-release formulation of bupropion.

Adverse Events Leading to Discontinuation of Treatment With WELLBUTRIN or WELLBUTRIN SR: In placebo-controlled clinical trials, 9% and 11% of patients treated with 300 and 400 mg/day, respectively, of the sustained-release formulation of bupropion and 4% of patients treated with placebo discontinued treatment due to adverse events. The specific adverse events in these trials that led to discontinuation in at least 1% of patients treated with either 300 mg/day or 400 mg/day of WELLBUTRIN SR, the sustained-release formulation of bupropion, and at a rate at least twice the placebo rate are listed in Table 6.

Table 6. Treatment Discontinuations Due to Adverse Events in Placebo-Controlled Trials for Major Depressive Disorder
Adverse Event Term | WELLBUTRIN SR; 300 mg/day; (n = 376) | WELLBUTRIN SR; 400 mg/day; (n = 114) | Placebo; (n = 385)
Rash | 2.4% | 0.9% | 0.0%
Nausea | 0.8% | 1.8% | 0.3%
Agitation | 0.3% | 1.8% | 0.3%
Migraine | 0.0% | 1.8% | 0.3%

In clinical trials with the immediate-release formulation of bupropion, 10% of patients and volunteers discontinued due to an adverse event. Events resulting in discontinuation, in addition to those listed above for the sustained-release formulation of bupropion, include vomiting, seizures, and sleep disturbances.

Adverse Events Occurring at an Incidence of 1% or More Among Patients Treated With WELLBUTRIN or WELLBUTRIN SR: Table 7 enumerates treatment-emergent adverse events that occurred among patients treated with 300 and 400 mg/day of the sustained-release formulation of bupropion and with placebo in controlled trials. Events that occurred in either the 300- or 400-mg/day group at an incidence of 1% or more and were more frequent than in the placebo group are included. Reported adverse events were classified using a COSTART-based Dictionary.

Accurate estimates of the incidence of adverse events associated with the use of any drug are difficult to obtain. Estimates are influenced by drug dose, detection technique, setting, physician judgments, etc. The figures cited cannot be used to predict precisely the incidence of untoward events in the course of usual medical practice where patient characteristics and other factors differ from those that prevailed in the clinical trials. These incidence figures also cannot be compared with those obtained from other clinical studies involving related drug products as each group of drug trials is conducted under a different set of conditions.

Finally, it is important to emphasize that the tabulation does not reflect the relative severity and/or clinical importance of the events. A better perspective on the serious adverse events associated with the use of bupropion is provided in the WARNINGS and PRECAUTIONS sections.

Table 7. Treatment-Emergent Adverse Events in Placebo-Controlled Trials [Adverse events that occurred in at least 1% of patients treated with either 300 or 400 mg/day of the sustained-release formulation of bupropion, but equally or more frequently in the placebo group, were: abnormal dreams, accidental injury, acne, appetite increased, back pain, bronchitis, dysmenorrhea, dyspepsia, flatulence, flu syndrome, hypertension, neck pain, respiratory disorder, rhinitis, and tooth disorder.] for Major Depressive Disorder
Body System/; Adverse Event | WELLBUTRIN SR; 300 mg/day; (n = 376) | WELLBUTRIN SR; 400 mg/day; (n = 114) | Placebo; (n = 385)
Body (General)
Headache | 26% | 25% | 23%
Infection | 8% | 9% | 6%
Abdominal pain | 3% | 9% | 2%
Asthenia | 2% | 4% | 2%
Chest pain | 3% | 4% | 1%
Pain | 2% | 3% | 2%
Fever | 1% | 2% | —
Cardiovascular
Palpitation | 2% | 6% | 2%
Flushing | 1% | 4% | —
Migraine | 1% | 4% | 1%
Hot flashes | 1% | 3% | 1%
Digestive
Dry mouth | 17% | 24% | 7%
Nausea | 13% | 18% | 8%
Constipation | 10% | 5% | 7%
Diarrhea | 5% | 7% | 6%
Anorexia | 5% | 3% | 2%
Vomiting | 4% | 2% | 2%
Dysphagia | 0% | 2% | 0%
Musculoskeletal
Myalgia | 2% | 6% | 3%
Arthralgia | 1% | 4% | 1%
Arthritis | 0% | 2% | 0%
Twitch | 1% | 2% | —
Nervous system
Insomnia | 11% | 16% | 6%
Dizziness | 7% | 11% | 5%
Agitation | 3% | 9% | 2%
Anxiety | 5% | 6% | 3%
Tremor | 6% | 3% | 1%
Nervousness | 5% | 3% | 3%
Somnolence | 2% | 3% | 2%
Irritability | 3% | 2% | 2%
Memory decreased | — | 3% | 1%
Paresthesia | 1% | 2% | 1%
Central nervous system stimulation | 2% | 1% | 1%
Respiratory
Pharyngitis | 3% | 11% | 2%
Sinusitis | 3% | 1% | 2%
Increased cough | 1% | 2% | 1%
Skin
Sweating | 6% | 5% | 2%
Rash | 5% | 4% | 1%
Pruritus | 2% | 4% | 2%
Urticaria | 2% | 1% | 0%
Special senses
Tinnitus | 6% | 6% | 2%
Taste perversion | 2% | 4% | —
Blurred vision or diplopia | 3% | 2% | 2%
Urogenital
Urinary frequency | 2% | 5% | 2%
Urinary urgency | — | 2% | 0%
Vaginal hemorrhage [Incidence based on the number of female patients.] | 0% | 2% | —
Urinary tract infection | 1% | 0% | —
— Hyphen denotes adverse events occurring in greater than 0 but less than 0.5% of patients.

Additional events to those listed in Table 7 that occurred at an incidence of at least 1% in controlled clinical trials of the immediate-release formulation of bupropion (300 to 600 mg/day) and that were numerically more frequent than placebo were: cardiac arrhythmias (5% vs 4%), hypertension (4% vs 2%), hypotension (3% vs 2%), tachycardia (11% vs 9%), appetite increase (4% vs 2%), dyspepsia (3% vs 2%), menstrual complaints (5% vs 1%), akathisia (2% vs 1%), impaired sleep quality (4% vs 2%), sensory disturbance (4% vs 3%), confusion (8% vs 5%), decreased libido (3% vs 2%), hostility (6% vs 4%), auditory disturbance (5% vs 3%), and gustatory disturbance (3% vs 1%).

Incidence of Commonly Observed Adverse Events in Controlled Clinical Trials:
Adverse events from Table 7 occurring in at least 5% of patients treated with the sustained-release formulation of bupropion and at a rate at least twice the placebo rate are listed below for the 300- and 400-mg/day dose groups.

300 mg/day of WELLBUTRIN SR: Anorexia, dry mouth, rash, sweating, tinnitus, and tremor.

400 mg/day of WELLBUTRIN SR: Abdominal pain, agitation, anxiety, dizziness, dry mouth, insomnia, myalgia, nausea, palpitation, pharyngitis, sweating, tinnitus, and urinary frequency.

Seasonal Affective Disorder: Adverse Events Leading to Discontinuation of Treatment With WELLBUTRIN XL: In placebo-controlled clinical trials, 9% of patients treated with WELLBUTRIN XL and 5% of patients treated with placebo discontinued treatment due to adverse events. The adverse events in these trials that led to discontinuation in at least 1% of patients treated with WELLBUTRIN XL and at a rate numerically greater than the placebo rate are insomnia (2% vs<1%) and headache (1% vs <1%).

Adverse Events Occurring at an Incidence of 2% or More Among Patients Treated With WELLBUTRIN XL: Table 8 enumerates treatment-emergent adverse events that occurred among patients treated with WELLBUTRIN XL for up to approximately 6 months in 3 placebo-controlled trials. Events that occurred at an incidence of 2% or more and were more frequent than in the placebo group are included. Reported adverse events were classified using a MedDRA-based Dictionary.

Accurate estimates of the incidence of adverse events associated with the use of any drug are difficult to obtain. Estimates are influenced by drug dose, detection technique, setting, physician judgments, etc. The figures cited cannot be used to predict precisely the incidence of untoward events in the course of usual medical practice where patient characteristics and other factors differ from those that prevailed in the clinical trials. These incidence figures also cannot be compared with those obtained from other clinical studies involving related drug products as each group of drug trials is conducted under a different set of conditions; e.g., different patient populations, different treatment durations.

Finally, it is important to emphasize that the tabulation does not reflect the relative severity and/or clinical importance of the events. A better perspective on the serious adverse events associated with the use of bupropion is provided in the WARNINGS and PRECAUTIONS sections.

Table 8. Treatment-Emergent Adverse Events [Adverse events that occurred in at least 2% of patients treated with WELLBUTRIN XL, but equally or more frequently in the placebo group, were: abdominal pain upper, arthralgia, back pain, diarrhea, dyspepsia, fatigue, gastroenteritis viral, hyperhidrosis, influenza, irritability, migraine, nasal congestion, neck pain, palpitations, pharyngolaryngeal pain, sinus congestion.] in Placebo-Controlled Trials of Seasonal Affective Disorder
System Organ Class/; Preferred Term | WELLBUTRIN XL; (n = 537) | Placebo; (n = 511)
Gastrointestinal Disorder
Dry Mouth | 26% | 15%
Nausea | 13% | 8%
Constipation | 9% | 2%
Flatulence | 6% | 3%
Abdominal pain | 2% | <1%
Nervous System Disorders
Headache | 34% | 26%
Dizziness | 6% | 5%
Tremor | 3% | <1%
Infections and Infestations
Nasopharyngitis | 13% | 12%
Upper respiratory tract infection | 9% | 8%
Sinusitis | 5% | 4%
Psychiatric Disorders
Insomnia | 20% | 13%
Anxiety | 7% | 5%
Abnormal dreams | 3% | 2%
Agitation | 2% | <1%
Musculoskeletal and Connective Tissue Disorders
Myalgia | 3% | 2%
Pain in extremity | 3% | 2%
Respiratory, Thoracic and Mediastinal Disorders
Cough | 4% | 3%
General Disorders and Administration Site Conditions
Feeling jittery | 3% | 2%
Skin and Subcutaneous Tissue Disorders
Rash | 3% | 2%
Metabolism and Nutrition Disorders
Decreased appetite | 4% | 1%
Reproductive System and Breast Disorders
Dysmenorrhea | 2% | <1%
Ear and Labyrinth Disorders
Tinnitus | 3% | <1%
Vascular Disorders
Hypertension | 2% | 0%

Incidence of Commonly Observed Adverse Events in Controlled Clinical Trials: Adverse events from Table 8 that occurred in at least 5% of patients treated with WELLBUTRIN XL and at a rate at least twice the placebo rate were constipation and flatulence.

Adverse Events During Taper or Following Discontinuation of WELLBUTRIN XL: Adverse events with onset during the 2 weeks following down-titration of WELLBUTRIN XL from 300 mg/day to 150 mg/day were reported by 14% of patients compared to 18% of patients who continued on placebo.

Adverse events with onset during the 2 weeks following discontinuation of WELLBUTRIN XL were reported by 9% of patients compared with 12% of patients following discontinuation of placebo.

Other Events Observed During the Clinical Development and Postmarketing Experience of Bupropion: In addition to the adverse events noted above, the following events have been reported in clinical trials and postmarketing experience with the sustained-release formulation of bupropion in depressed patients and in nondepressed smokers, as well as in clinical trials and postmarketing clinical experience with the immediate-release formulation of bupropion.

Adverse events for which frequencies are provided below occurred in clinical trials with the sustained-release formulation of bupropion. The frequencies represent the proportion of patients who experienced a treatment-emergent adverse event on at least one occasion in placebo-controlled studies for depression (n = 987) or smoking cessation (n = 1,013), or patients who experienced an adverse event requiring discontinuation of treatment in an open-label surveillance study with the sustained-release formulation of bupropion (n = 3,100). All treatment-emergent adverse events are included except those listed in Tables 2 through 8, those events listed in other safety-related sections, those adverse events subsumed under COSTART terms that are either overly general or excessively specific so as to be uninformative, those events not reasonably associated with the use of the drug, and those events that were not serious and occurred in fewer than 2 patients. Events of major clinical importance are described in the WARNINGS and PRECAUTIONS sections of the labeling.

Events are further categorized by body system and listed in order of decreasing frequency according to the following definitions of frequency: Frequent adverse events are defined as those occurring in at least 1/100 patients. Infrequent adverse events are those occurring in 1/100 to 1/1,000 patients, while rare events are those occurring in less than 1/1,000 patients.

Adverse events for which frequencies are not provided occurred in clinical trials or postmarketing experience with bupropion. Only those adverse events not previously listed for sustained-release bupropion are included. The extent to which these events may be associated with WELLBUTRIN XL is unknown.

Body (General): Infrequent were chills, facial edema, musculoskeletal chest pain, and photosensitivity. Rare was malaise. Also observed were arthralgia, myalgia, and fever with rash and other symptoms suggestive of delayed hypersensitivity. These symptoms may resemble serum sickness (see PRECAUTIONS).

Cardiovascular: Infrequent were postural hypotension, stroke, tachycardia, and vasodilation. Rare was syncope. Also observed were complete atrioventricular block, extrasystoles, hypotension, hypertension (in some cases severe, see PRECAUTIONS), myocardial infarction, phlebitis, and pulmonary embolism.

Digestive: Infrequent were abnormal liver function, bruxism, gastric reflux, gingivitis, glossitis, increased salivation, jaundice, mouth ulcers, stomatitis, and thirst. Rare was edema of tongue. Also observed were colitis, esophagitis, gastrointestinal hemorrhage, gum hemorrhage, hepatitis, intestinal perforation, liver damage, pancreatitis, and stomach ulcer.

Endocrine: Also observed were hyperglycemia, hypoglycemia, and syndrome of inappropriate antidiuretic hormone.

Hemic and Lymphatic: Infrequent was ecchymosis. Also observed were anemia, leukocytosis, leukopenia, lymphadenopathy, pancytopenia, and thrombocytopenia. Altered PT and/or INR, infrequently associated with hemorrhagic or thrombotic complications, were observed when bupropion was coadministered with warfarin.

Metabolic and Nutritional: Infrequent were edema and peripheral edema. Also observed was glycosuria.

Musculoskeletal: Infrequent were leg cramps. Also observed were muscle rigidity/fever/rhabdomyolysis and muscle weakness.

Nervous System: Infrequent were abnormal coordination, decreased libido, depersonalization, dysphoria, emotional lability, hostility, hyperkinesia, hypertonia, hypesthesia, suicidal ideation, and vertigo. Rare were amnesia, ataxia, derealization, and hypomania. Also observed were abnormal electroencephalogram (EEG), aggression, akinesia, aphasia, coma, completed suicide, delirium, delusions, dysarthria, dyskinesia, dystonia, euphoria, extrapyramidal syndrome, hallucinations, hypokinesia, increased libido, manic reaction, neuralgia, neuropathy, paranoid ideation, restlessness, suicide attempt, and unmasking tardive dyskinesia.

Respiratory: Rare was bronchospasm. Also observed was pneumonia.

Skin: Rare was maculopapular rash. Also observed were alopecia, angioedema, exfoliative dermatitis, and hirsutism.

Special Senses: Infrequent were accommodation abnormality and dry eye. Also observed were deafness, diplopia, increased intraocular pressure, and mydriasis.

Urogenital: Infrequent were impotence, polyuria, and prostate disorder. Also observed were abnormal ejaculation, cystitis, dyspareunia, dysuria, gynecomastia, menopause, painful erection, salpingitis, urinary incontinence, urinary retention, and vaginitis.

DRUG ABUSE AND DEPENDENCE

CONTROLLED SUBSTANCE

Controlled Substance Class: Bupropion is not a controlled substance.

Humans: Controlled clinical studies of bupropion (immediate-release formulation) conducted in normal volunteers, in subjects with a history of multiple drug abuse, and in depressed patients showed some increase in motor activity and agitation/excitement.

In a population of individuals experienced with drugs of abuse, a single dose of 400 mg of bupropion produced mild amphetamine-like activity as compared to placebo on the Morphine-Benzedrine Subscale of the Addiction Research Center Inventories (ARCI), and a score intermediate between placebo and amphetamine on the Liking Scale of the ARCI. These scales measure general feelings of euphoria and drug desirability.

Findings in clinical trials, however, are not known to reliably predict the abuse potential of drugs. Nonetheless, evidence from single-dose studies does suggest that the recommended daily dosage of bupropion when administered in divided doses is not likely to be especially reinforcing to amphetamine or stimulant abusers. However, higher doses that could not be tested because of the risk of seizure might be modestly attractive to those who abuse stimulant drugs.

Animals: Studies in rodents and primates have shown that bupropion exhibits some pharmacologic actions common to psychostimulants. In rodents, it has been shown to increase locomotor activity, elicit a mild stereotyped behavioral response, and increase rates of responding in several schedule-controlled behavior paradigms. In primate models to assess the positive reinforcing effects of psychoactive drugs, bupropion was self-administered intravenously. In rats, bupropion produced amphetamine-like and cocaine-like discriminative stimulus effects in drug discrimination paradigms used to characterize the subjective effects of psychoactive drugs.

OVERDOSAGE

Human Overdose Experience: Overdoses of up to 30 g or more of bupropion have been reported. Seizure was reported in approximately one third of all cases. Other serious reactions reported with overdoses of bupropion alone included hallucinations, loss of consciousness, sinus tachycardia, and ECG changes such as conduction disturbances (including QRS prolongation) or arrhythmias. Fever, muscle rigidity, rhabdomyolysis, hypotension, stupor, coma, and respiratory failure have been reported mainly when bupropion was part of multiple drug overdoses.

Although most patients recovered without sequelae, deaths associated with overdoses of bupropion alone have been reported in patients ingesting large doses of the drug. Multiple uncontrolled seizures, bradycardia, cardiac failure, and cardiac arrest prior to death were reported in these patients.

Overdosage Management: Ensure an adequate airway, oxygenation, and ventilation. Monitor cardiac rhythm and vital signs. EEG monitoring is also recommended for the first 48 hours post-ingestion. General supportive and symptomatic measures are also recommended. Induction of emesis is not recommended.

Activated charcoal should be administered. There is no experience with the use of forced diuresis, dialysis, hemoperfusion, or exchange transfusion in the management of bupropion overdoses. No specific antidotes for bupropion are known.

Due to the dose-related risk of seizures with WELLBUTRIN XL, hospitalization following suspected overdose should be considered. Based on studies in animals, it is recommended that seizures be treated with intravenous benzodiazepine administration and other supportive measures, as appropriate.

In managing overdosage, consider the possibility of multiple drug involvement. The physician should consider contacting a poison control center for additional information on the treatment of any overdose. Telephone numbers for certified poison control centers are listed in the Physicians' Desk Reference (PDR).

DOSAGE AND ADMINISTRATION

General Dosing Considerations: It is particularly important to administer WELLBUTRIN XL in a manner most likely to minimize the risk of seizure (see WARNINGS). Gradual escalation in dosage is also important if agitation, motor restlessness, and insomnia, often seen during the initial days of treatment, are to be minimized. If necessary, these effects may be managed by temporary reduction of dose or the short-term administration of an intermediate to long-acting sedative hypnotic. A sedative hypnotic usually is not required beyond the first week of treatment. Insomnia may also be minimized by avoiding bedtime doses. If distressing, untoward effects supervene, dose escalation should be stopped. WELLBUTRIN XL tablets should be swallowed whole and not crushed, divided, or chewed as this may lead to an increased risk of adverse effects including seizures. WELLBUTRIN XL may be taken without regard to meals.

Major Depressive Disorder: Initial Treatment: The usual adult target dose for WELLBUTRIN XL is 300 mg/day, given once daily in the morning. Dosing with WELLBUTRIN XL should begin at 150 mg/day given as a single daily dose in the morning. If the 150-mg initial dose is adequately tolerated, an increase to the 300-mg/day target dose, given as once daily, may be made as early as day 4 of dosing. There should be an interval of at least 24 hours between successive doses.

Increasing the Dosage Above 300 mg/day: As with other antidepressants, the full antidepressant effect of WELLBUTRIN XL may not be evident until 4 weeks of treatment or longer. An increase in dosage to the maximum of 450 mg/day, given as a single dose, may be considered for patients in whom no clinical improvement is noted after several weeks of treatment at 300 mg/day.

Maintenance Treatment: It is generally agreed that acute episodes of depression require several months or longer of sustained pharmacological therapy beyond response to the acute episode. It is unknown whether or not the dose of WELLBUTRIN XL needed for maintenance treatment is identical to the dose needed to achieve an initial response. Patients should be periodically reassessed to determine the need for maintenance treatment and the appropriate dose for such treatment.

Seasonal Affective Disorder: For the prevention of seasonal major depressive episodes associated with seasonal affective disorder, WELLBUTRIN XL should generally be initiated in the autumn prior to the onset of depressive symptoms. Treatment should continue through the winter season and should be tapered and discontinued in early spring. The timing of initiation and duration of treatment should be individualized based on the patient's historical pattern of seasonal major depressive episodes. Patients whose seasonal depressive episodes are infrequent or not associated with significant impairment should not generally be treated prophylactically.

Dosing with WELLBUTRIN XL should begin at 150 mg/day given as a single daily dose in the morning. If the 150-mg initial dose is adequately tolerated, the dose of WELLBUTRIN XL should be increased to the 300-mg/day dose after 1 week. If the 300-mg dose is not adequately tolerated, the dose can be reduced to 150 mg/day. The usual adult target dose for WELLBUTRIN XL is 300 mg/day, given once daily in the morning.

For patients taking 300 mg/day during the autumn-winter season, the dose should be tapered to 150 mg/day for 2 weeks prior to discontinuation.

Doses of WELLBUTRIN XL above 300 mg/day have not been studied for the prevention of seasonal major depressive episodes.

Switching Patients from WELLBUTRIN Tablets or from WELLBUTRIN SR Sustained-Release Tablets: When switching patients from WELLBUTRIN Tablets to WELLBUTRIN XL or from WELLBUTRIN SR Sustained-Release Tablets to WELLBUTRIN XL, give the same total daily dose when possible. Patients who are currently being treated with WELLBUTRIN Tablets at 300 mg/day (for example, 100 mg 3 times a day) may be switched to WELLBUTRIN XL 300 mg once daily. Patients who are currently being treated with WELLBUTRIN SR Sustained-Release Tablets at 300 mg/day (for example, 150 mg twice daily) may be switched to WELLBUTRIN XL 300 mg once daily.

Dosage Adjustment for Patients With Impaired Hepatic Function: WELLBUTRIN XL should be used with extreme caution in patients with severe hepatic cirrhosis. The dose should not exceed 150 mg every other day in these patients. WELLBUTRIN XL should be used with caution in patients with hepatic impairment (including mild-to-moderate hepatic cirrhosis) and a reduced frequency and/or dose should be considered in patients with mild-to-moderate hepatic cirrhosis (see CLINICAL PHARMACOLOGY, WARNINGS, and PRECAUTIONS).

Dosage Adjustment for Patients With Impaired Renal Function: WELLBUTRIN XL should be used with caution in patients with renal impairment and a reduced frequency and/or dose should be considered (see CLINICAL PHARMACOLOGY and PRECAUTIONS).

HOW SUPPLIED

WELLBUTRIN XL Extended-Release Tablets, 300 mg of bupropion hydrochloride, are creamy-white to pale yellow, round, tablets printed with "WELLBUTRIN XL 300" in:

Bottles of 30 - NDC 16590-246-30

STORAGE AND HANDLING

Store at 25°C (77°F); excursions permitted to 15-30°C (59-86°F) [see USP Controlled Room Temperature].

Relabeling and Repackaging by:
STAT Rx USA LLC
Gainesville, GA 30501

MEDICATION GUIDE

WELLBUTRIN XL®* (WELL byu-trin)

(bupropion hydrochloride extended-release tablets)

Read this Medication Guide carefully before you start using WELLBUTRIN XL and each time you get a refill. There may be new information. This information does not take the place of talking with your doctor about your medical condition or your treatment. If you have any questions about WELLBUTRIN XL, ask your doctor or pharmacist.

IMPORTANT: Be sure to read the three sections of this Medication Guide. The first section is about the risk of suicidal thoughts and actions with antidepressant medicines, the second section is about the risk of changes in thinking and behavior, depression and suicidal thoughts or actions with medicines used to quit smoking; and the third section is entitled " What Other Important Information Should I Know About WELLBUTRIN XL?"

Antidepressant Medicines, Depression and Other Serious Mental Illnesses, and Suicidal Thoughts or Actions

This section of the Medication Guide is only about the risk of suicidal thoughts and actions with antidepressant medicines. Talk to your doctor or your family member's healthcare provider about:

- all risks and benefits of treatment with antidepressant medicines
- all treatment choices for depression or other serious mental illness

What is the most important information I should know about antidepressant medicines, depression and other serious mental illnesses, and suicidal thoughts or actions?

1. Antidepressant medicines may increase suicidal thoughts or actions in some children, teenagers, and young adults within the first few months of treatment.
2. Depression and other serious mental illnesses are the most important causes of suicidal thoughts and actions. Some people may have a particularly high risk of having suicidal thoughts or actions. These include people who have (or have a family history of) bipolar illness (also called manic-depressive illness) or suicidal thoughts or actions.
3. How can I watch for and try to prevent suicidal thoughts and actions in myself or a family member?
  - Pay close attention to any changes, especially sudden changes, in mood, behaviors, thoughts, or feelings. This is very important when an antidepressant medicine is started or when the dose is changed.
  - Call the healthcare provider right away to report new or sudden changes in mood, behavior, thoughts, or feelings.
  - Keep all follow-up visits with the healthcare provider as scheduled. Call the healthcare provider between visits as needed, especially if you have concerns about symptoms.

Call a healthcare provider right away if you or your family member has any of the following symptoms, especially if they are new, worse, or worry you:

- thoughts about suicide or dying
- attempts to commit suicide
- new or worse depression
- new or worse anxiety
- feeling very agitated or restless
- panic attacks

- trouble sleeping (insomnia)
- new or worse irritability
- acting aggressive, being angry, or violent
- acting on dangerous impulses
- an extreme increase in activity and talking (mania)
- other unusual changes in behavior or mood

What else do I need to know about antidepressant medicines?

- Never stop an antidepressant medicine without first talking to a healthcare provider. Stopping an antidepressant medicine suddenly can cause other symptoms.
- Antidepressants are medicines used to treat depression and other illnesses. It is important to discuss all the risks of treating depression and also the risks of not treating it. Patients and their families or other caregivers should discuss all treatment choices with the healthcare provider, not just the use of antidepressants.
- Antidepressant medicines have other side effects. Talk to the healthcare provider about the side effects of the medicine prescribed for you or your family member.
- Antidepressant medicines can interact with other medicines. Know all of the medicines that you or your family member takes. Keep a list of all medicines to show the healthcare provider. Do not start new medicines without first checking with your healthcare provider.
- Not all antidepressant medicines prescribed for children are FDA approved for use in children. Talk to your child's healthcare provider for more information.

WELLBUTRIN XL has not been studied in children under the age of 18 and is not approved for use in children and teenagers.

Quitting Smoking, Quit-Smoking Medications, Changes in Thinking and Behavior, Depression, and Suicidal Thoughts or Actions

This section of the Medication Guide is only about the risk of changes in thinking and behavior, depression and suicidal thoughts or actions with drugs used to quit smoking.

Although WELLBUTRIN XL is not a treatment for quitting smoking, it contains the same active ingredient (bupropion hydrochloride) as ZYBAN® which is used to help patients quit smoking.

Some people have had changes in behavior, hostility, agitation, depression, suicidal thoughts or actions while taking bupropion to help them quit smoking. These symptoms can develop during treatment with bupropion or after stopping treatment with bupropion.

If you, your family member, or your caregiver notice agitation, hostility, depression or changes in thinking or behavior that are not typical for you, or you have any of the following symptoms, stop taking bupropion and call your healthcare provider right away:

- thoughts about suicide or dying
- attempts to commit suicide
- new or worse depression
- new or worse anxiety
- panic attacks
- feeling very agitated or restless
- acting aggressive, being angry, or violent
- acting on dangerous impulses

- an extreme increase in activity and talking (mania)
- abnormal thoughts or sensations
- seeing or hearing things that are not there (hallucinations)
- feeling people are against you (paranoia)
- feeling confused
- other unusual changes in behavior or mood

When you try to quit smoking, with or without bupropion, you may have symptoms that may be due to nicotine withdrawal, including urge to smoke, depressed mood, trouble sleeping, irritability, frustration, anger, feeling anxious, difficulty concentrating, restlessness, decreased heart rate, and increased appetite or weight gain. Some people have even experienced suicidal thoughts when trying to quit smoking without medication. Sometimes quitting smoking can lead to worsening of mental health problems that you already have, such as depression.

Before taking bupropion, tell your healthcare provider if you have ever had depression or other mental illnesses. You should also tell your doctor about any symptoms you had during other times you tried to quit smoking, with or without bupropion.

What Other Important Information Should I Know About WELLBUTRIN XL?

- Seizures: There is a chance of having a seizure (convulsion, fit) with WELLBUTRIN XL, especially in people:
  - with certain medical problems.
  - who take certain medicines.

The chance of having seizures increases with higher doses of WELLBUTRIN XL. For more information, see the sections " Who should not take WELLBUTRIN XL?" and " What should I tell my doctor before using WELLBUTRIN XL?" Tell your doctor about all of your medical conditions and all the medicines you take. Do not take any other medicines while you are using WELLBUTRIN XL unless your doctor has said it is okay to take them.

If you have a seizure while taking WELLBUTRIN XL, stop taking the tablets and call your doctor right away. Do not take WELLBUTRIN XL again if you have a seizure.

- High blood pressure (hypertension): Some people get high blood pressure, that can be severe, while taking Wellbutrin XL. The chance of high blood pressure may be higher if you also use nicotine replacement therapy (such as a nicotine patch) to help you stop smoking.
- Severe allergic reactions: Some people have severe allergic reactions to Wellbutrin XL. Stop taking Wellbutrin XL and call your doctor right away if you get a rash, itching, hives, fever, swollen lymph glands, painful sores in the mouth or around the eyes, swelling of the lips or tongue, chest pain, or have trouble breathing. These could be signs of a serious allergic reaction.
- Unusual thoughts or behaviors: Some patients have unusual thoughts or behaviors while taking Wellbutrin XL, including delusions (believe you are someone else), hallucinations (seeing or hearing things that are not there), paranoia (feeling that people are against you), or feeling confused. If this happens to you, call your doctor.

What is WELLBUTRIN XL?

WELLBUTRIN XL is a prescription medicine used to treat adults with a certain type of depression called major depressive disorder and for prevention of autumn-winter seasonal depression (seasonal affective disorder).

Who should not take WELLBUTRIN XL?

Do not take WELLBUTRIN XL if you:

- have or had a seizure disorder or epilepsy.
- are taking ZYBAN® (used to help people stop smoking) or any other medicines that contain bupropion hydrochloride, such as WELLBUTRIN®* Tablets or WELLBUTRIN SR, Sustained-Release Tablets. Bupropion is the same active ingredient that is in WELLBUTRIN XL.
- drink a lot of alcohol and abruptly stop drinking, or use medicines called sedatives (these make you sleepy) or benzodiazepines and you stop using them all of a sudden.
- have taken within the last 14 days medicine for depression called a monoamine oxidase inhibitor (MAOI), such as NARDIL®* (phenelzine sulfate), PARNATE®* (tranylcypromine sulfate), or MARPLAN®* (isocarboxazid).
- have or had an eating disorder such as anorexia nervosa or bulimia.
- are allergic to the active ingredient in WELLBUTRIN XL, bupropion, or to any of the inactive ingredients. See the end of this leaflet for a complete list of ingredients in WELLBUTRIN XL.

What should I tell my doctor before using WELLBUTRIN XL?

- Tell your doctor if you have ever had depression, suicidal thoughts or actions, or other mental health problems. See "Antidepressant Medicines, Depression and Other Serious Mental Illnesses, and Suicidal Thoughts or Actions."
- Tell your doctor about your other medical conditions, including if you:
  - are pregnant or plan to become pregnant. It is not known if WELLBUTRIN XL can harm your unborn baby.
  - are breastfeeding. WELLBUTRIN XL passes through your milk. It is not known if WELLBUTRIN XL can harm your baby.
  - have liver problems, especially cirrhosis of the liver.
  - have kidney problems.
  - have an eating disorder such as anorexia nervosa or bulimia.
  - have had a head injury.
  - have had a seizure (convulsion, fit).
  - have a tumor in your nervous system (brain or spine).
  - have had a heart attack, heart problems, or high blood pressure.
  - are a diabetic taking insulin or other medicines to control your blood sugar.
  - drink a lot of alcohol.
  - abuse prescription medicines or street drugs.
- Tell your doctor about all the medicines you take, including prescription and non-prescription medicines, vitamins and herbal supplements. Many medicines increase your chances of having seizures or other serious side effects if you take them while you are using WELLBUTRIN XL.

How should I take WELLBUTRIN XL?

- Take WELLBUTRIN XL exactly as prescribed by your doctor.
- Do not chew, cut, or crush WELLBUTRIN XL tablets. If you do, the medicine will be released into your body too quickly. If this happens you may be more likely to get side effects including seizures. You must swallow the tablets whole. Tell your doctor if you cannot swallow medicine tablets.
- Take WELLBUTRIN XL at the same time each day.
- Take your doses of WELLBUTRIN XL at least 24 hours apart.
- You may take WELLBUTRIN XL with or without food.
- If you miss a dose, do not take an extra tablet to make up for the dose you forgot. Wait and take your next tablet at the regular time. This is very important. Too much WELLBUTRIN XL can increase your chance of having a seizure.
- If you take too much WELLBUTRIN XL, or overdose, call your local emergency room or poison control center right away.
- The WELLBUTRIN XL tablet is covered by a shell that slowly releases the medicine inside your body. You may notice something in your stool that looks like a tablet. This is normal. This is the empty shell passing from your body.
- Do not take any other medicines while using WELLBUTRIN XL unless your doctor has told you it is okay.
- If you are taking WELLBUTRIN XL for the treatment of major depressive disorder, it may take several weeks for you to feel that WELLBUTRIN XL is working. Once you feel better, it is important to keep taking WELLBUTRIN XL exactly as directed by your doctor. Call your doctor if you do not feel WELLBUTRIN XL is working for you.
- If you are taking WELLBUTRIN XL for the prevention of seasonal major depressive episodes associated with seasonal affective disorder, it is important to keep taking WELLBUTRIN XL through the autumn-winter season, or as directed by your doctor.
- Do not change your dose or stop taking WELLBUTRIN XL without talking with your doctor first.

What should I avoid while taking WELLBUTRIN XL?

- Do not drink a lot of alcohol while taking WELLBUTRIN XL. If you usually drink a lot of alcohol, talk with your doctor before suddenly stopping. If you suddenly stop drinking alcohol, you may increase your chance of having seizures.
- Do not drive a car or use heavy machinery until you know how WELLBUTRIN XL affects you. WELLBUTRIN XL can impair your ability to perform these tasks.

What are possible side effects of WELLBUTRIN XL?

WELLBUTRIN XL can cause serious side effects. Read this entire Medication Guide for more information about these serious side effects.

Common side effects reported in studies of major depressive disorder include weight loss, loss of appetite, dry mouth, skin rash, sweating, ringing in the ears, shakiness, stomach pain, agitation, anxiety, dizziness, trouble sleeping, muscle pain, nausea, fast heartbeat, sore throat, and urinating more often. In studies of seasonal affective disorder, common side effects included weight loss, constipation, and gas.

If you have nausea, take your medicine with food. If you have trouble sleeping, do not take your medicine too close to bedtime.

These are not all the side effects of WELLBUTRIN XL. For a complete list, ask your doctor or pharmacist.

Call your doctor for medical advice about side effects. You may report side effects to FDA at 1-800-FDA-1088 or BTA Pharmaceuticals at 866-246-8245 (opt. 3).

How should I store WELLBUTRIN XL?

- Store WELLBUTRIN XL at room temperature. Store out of direct sunlight. Keep WELLBUTRIN XL in its tightly closed bottle.
- WELLBUTRIN XL tablets may have an odor.

General Information about WELLBUTRIN XL.

- Medicines are sometimes prescribed for purposes other than those listed in a Medication Guide. Do not use WELLBUTRIN XL for a condition for which it was not prescribed. Do not give WELLBUTRIN XL to other people, even if they have the same symptoms you have. It may harm them. Keep WELLBUTRIN XL out of the reach of children.
- If you take a urine drug screening test, WELLBUTRIN XL may make the test result positive for amphetamines. If you tell the person giving you the drug screening test that you are taking WELLBUTRIN XL, they can do a more specific drug screening test that should not have this problem.

This Medication Guide summarizes important information about WELLBUTRIN XL. For more information, talk with your doctor. You can ask your doctor or pharmacist for information about WELLBUTRIN XL that is written for health professionals or call 866-246-8245 (opt. 3).

What are the ingredients in WELLBUTRIN XL?

Active ingredient: bupropion hydrochloride.

Inactive ingredients: ethylcellulose aqueous dispersion, glyceryl behenate, methacrylic acid copolymer dispersion, polyvinyl alcohol, polyethylene glycol, povidone, silicon dioxide, and triethyl citrate. The tablets are printed with edible black ink.

*The following are registered trademarks of their respective manufacturers: WELLBUTRIN® and WELLBUTRIN XL®/GlaxoSmithKline; ZYBAN® /GlaxoSmithKline; PARNATE® / GlaxoSmithKline; NARDIL®/Warner Lambert Company; MARPLAN®/ Validus Pharmaceuticals LLC; KALETRA® /Abbott Laboratories.

Rx Only

This Medication Guide has been approved by the U.S. Food and Drug Administration.

Manufactured by:
Biovail Corporation
Mississauga, ON L5N 8M5, Canada

For:
BTA Pharmaceuticals, Inc. (subsidiary of Biovail Corporation)
Bridgewater, NJ 08807

Rev. 06/11

Relabeling and Repackaging by:

STAT Rx USA LLC

Gainesville, GA 30501